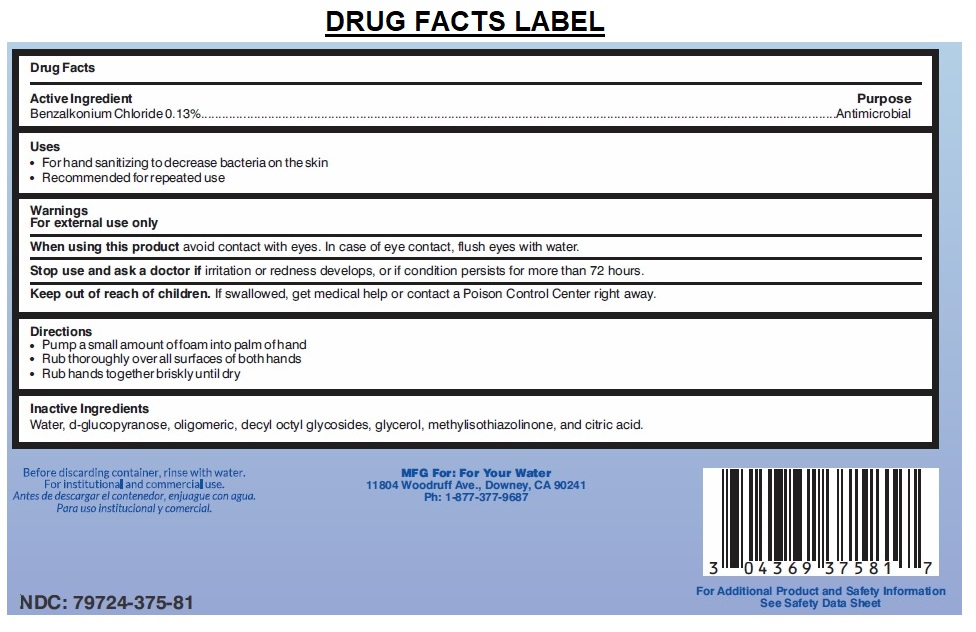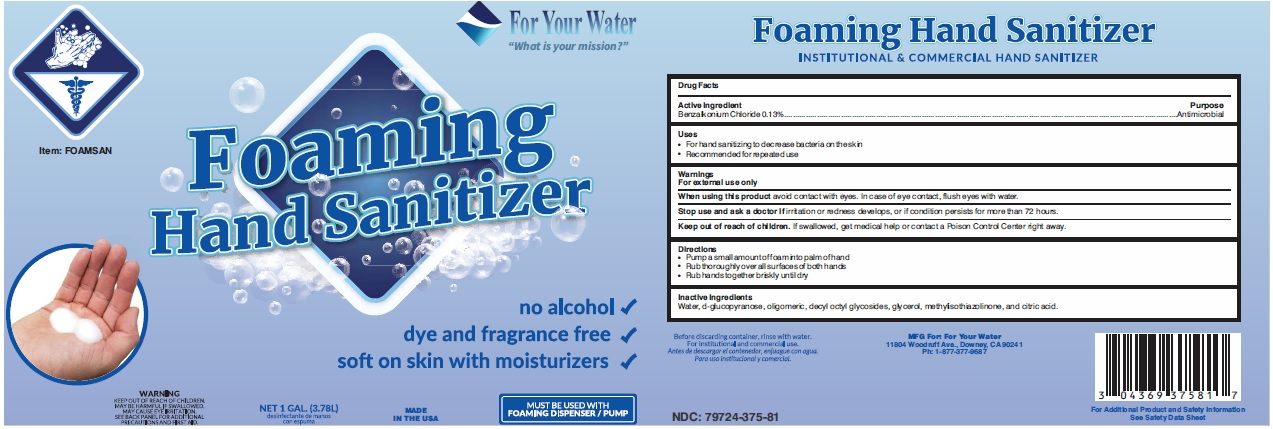 DRUG LABEL: Foaming Hand Sanitizer
NDC: 79724-375 | Form: LIQUID
Manufacturer: Specialty Water Resources, Llc
Category: otc | Type: HUMAN OTC DRUG LABEL
Date: 20200723

ACTIVE INGREDIENTS: BENZALKONIUM CHLORIDE 0.0013 mg/1 mL
INACTIVE INGREDIENTS: WATER; 2,3 DI-O-METHYL-D-GLUCOSE; CAPRYL OLIGOGLUCOSIDE; CAPRYLYL/CAPRYL OLIGOGLUCOSIDE; GLYCERIN; METHYLISOTHIAZOLINONE; CITRIC ACID MONOHYDRATE

For Your Water Foaming Hand Sanitizer

Active Ingredient

Benzalkonium Chloride 0.13%

Purpose

Antimicrobial

Uses

• For hand sanitizing to decrease bacteria on the skin
• Recommended for repeated use

Warnings

For external use only
When using this product avoid contact with eyes. In case of eye contact, flush eyes with water.

Stop use and ask a doctor if irritation or redness develops, or if condition persists for more than 72 hours.

Keep out of reach of children. If swallowed, get medical help or contact a Poison Control Center right away.

Directions

• Pump a small amount of foam into palm of hand
• Rub thoroughly over all surfaces of both hands
• Rub hands together briskly until dry

Inactive Ingredients

Water, d-glucopyranose, oligomeric, decyl octyl glycosides, glycerol, methylisothiazolinone, and citric acid.

For Your Water

"What is your mission?"

no alcohol

dye and fragrance free

soft on skin with moisturizers

MUST BE USED WITH FOAMING DISPENSER / PUMP

MADE IN THE USA

WARNING

KEEP OUT OF REACH OF CHILDREN.

MAY BE HARMFUL IF SWALLOWED.

MAY CAUSE EYE IRRITATION.

SEE BACK PANEL FOR ADDITIONAL PRECAUTIONS AND FIRST AID.

INSTITUTIONAL & COMMERCIAL HAND SANITIZER

Before discarding container, rinse with water.

For institutional and commercial use.

MFG For: For Your Water

11804 Woodruff Ave., Downey, CA 90241

Ph: 1-877-377-9687

For Additional Product and Safety Information
See Safety Data Sheet